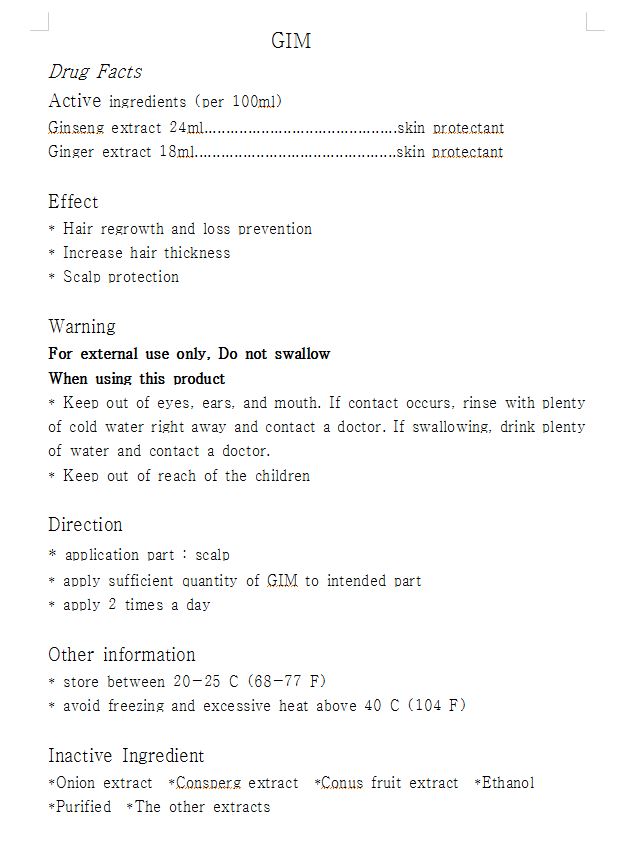 DRUG LABEL: GIM
NDC: 62085-1001 | Form: LIQUID
Manufacturer: Hee Dae Gim
Category: otc | Type: HUMAN OTC DRUG LABEL
Date: 20181128

ACTIVE INGREDIENTS: ASIAN GINSENG 24 g/100 mL
INACTIVE INGREDIENTS: GINGER; ANGELICA GIGAS ROOT; ASTRAGALUS PROPINQUUS ROOT; WATER

Drug Facts

Active Ingredient

Active Ingredients: Ginseng Extract 24%, Ginger Extract 18%

Inactive Ingredients

Inactive Ingredients: onion ext, conus fruit ext, consperg ext, angelica gigas ext, magnolia vine ext, astragalus membranaceus ext, ethanol, purified water

Purpose

Scalp protectant (hair growth and loss prevention)

Keep out of reach of children

Directions

application part: scalp

apply sufficient quantity of GIM to intended part

apply 2 times a day

Warnings

For external use only, Do not swallow

When using this product

Keep out of eyes, ears, and mouth. If contact occurs, rinse with plenty of cold water right away and contact a doctor.

If swallowing, drink plenty of water and contact a doctor

Directions

same as the above